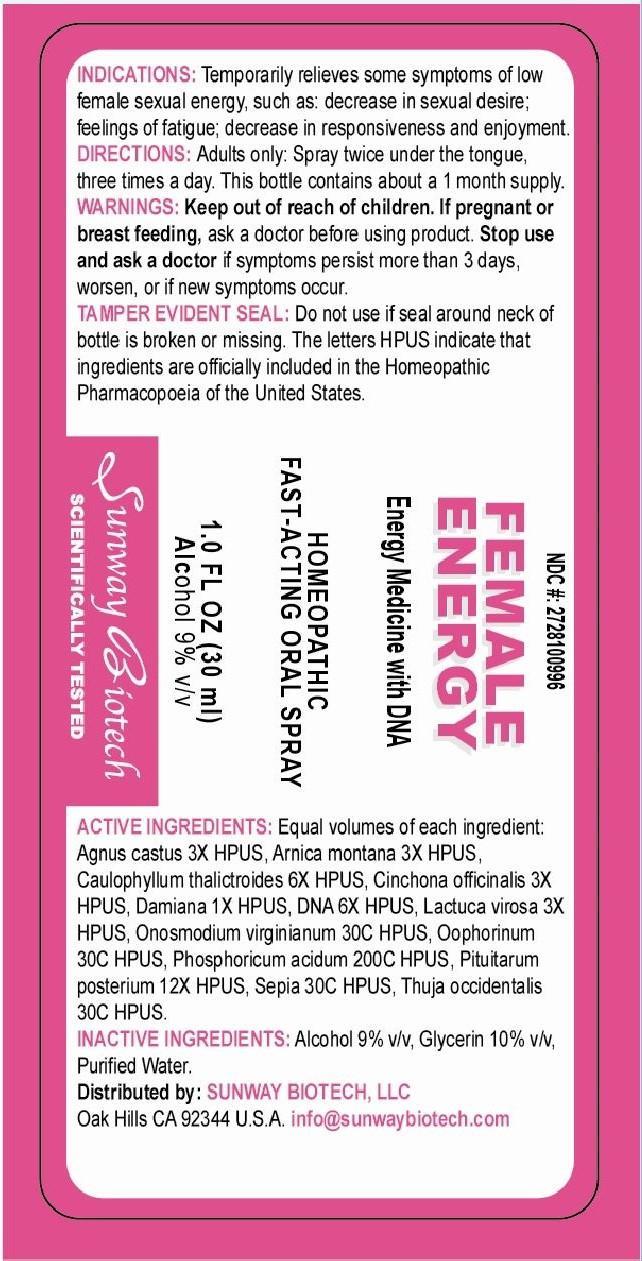 DRUG LABEL: Female Energy
NDC: 55138-012 | Form: SPRAY
Manufacturer: Integra Health International, S.A. de C.V.
Category: homeopathic | Type: HUMAN OTC DRUG LABEL
Date: 20140807

ACTIVE INGREDIENTS: CHASTE TREE 1.5 [hp_C]/1 mg; ARNICA MONTANA 1.5 [hp_C]/1 mg; CAULOPHYLLUM THALICTROIDES ROOT 3 [hp_C]/1 mg; CINCHONA OFFICINALIS BARK 1.5 [hp_C]/1 mg; TURNERA DIFFUSA LEAFY TWIG 0.5 [hp_C]/1 mg; HERRING SPERM DNA 3 [hp_C]/1 mg; LACTUCA VIROSA 1.5 [hp_C]/1 mg; ONOSMODIUM VIRGINIANUM WHOLE 30 [hp_C]/1 mg; SUS SCROFA OVARY 30 [hp_C]/1 mg; PHOSPHORIC ACID 200 [hp_C]/1 mg; SUS SCROFA PITUITARY GLAND 6 [hp_C]/1 mg; SEPIA OFFICINALIS JUICE 30 [hp_C]/1 mg; THUJA OCCIDENTALIS LEAFY TWIG 30 [hp_C]/1 mg
INACTIVE INGREDIENTS: ALCOHOL; GLYCERIN; WATER

Active Ingredients: equal volumes of each ingredient:

agnus castus 3x HPUS, arnica montana 3X HPUS, caulophyllum thalictroides 6X HPUS, cinchona officinalis 3X HPUS, damiana 1X HPUS, DNA 6X HPUS, lactuca virosa 3X HPUS, onosmodium virginianum 30C HPUS, oophorinum 30C HPUS, phosphoricum acidum 200C HPUS, pituitarium posterium 12X HPUS, sepia 30C HPUS, thuja occidentalis 30C HPUS.

PURPOSE

Female Energy

Energy Medicine with DINA

Homeopathic Fast-Acting Oral Spray

1.0 Fl Oz (30 ml)

Alcohol 9% v/v

Sunway Biotech

Scientifically Tested

Keep out of reach of children.

DOSAGE AND ADMINISTRATION

Directions: Adults only: Spray twice under the tongue, three times a day. This bottle contains about a 1 month supply.

WARNINGS

If pregnant or breast feeding, ask a doctor before using product. Stop use and ask a doctor if symptoms persist more than 3 days, worsen, or if new symptoms occur.

Tamper Evident Seal: Do not use if seal around neck of bottle is broken or missing. The letter HPUS indicate that ingredients are officially included in the Homeopathic Pharmacopoeia of the United States.

INDICATIONS AND USAGE

Indications: Temporarily relieves some symptoms of low female sexual energy, such as: decrease in sexual desire; feelings of fatigue; decrease in responsiveness and enjoyment.

INACTIVE INGREDIENT

Inactive Ingredients: Alcohol 9% v/v, glycerin 10% v/v, purified water.